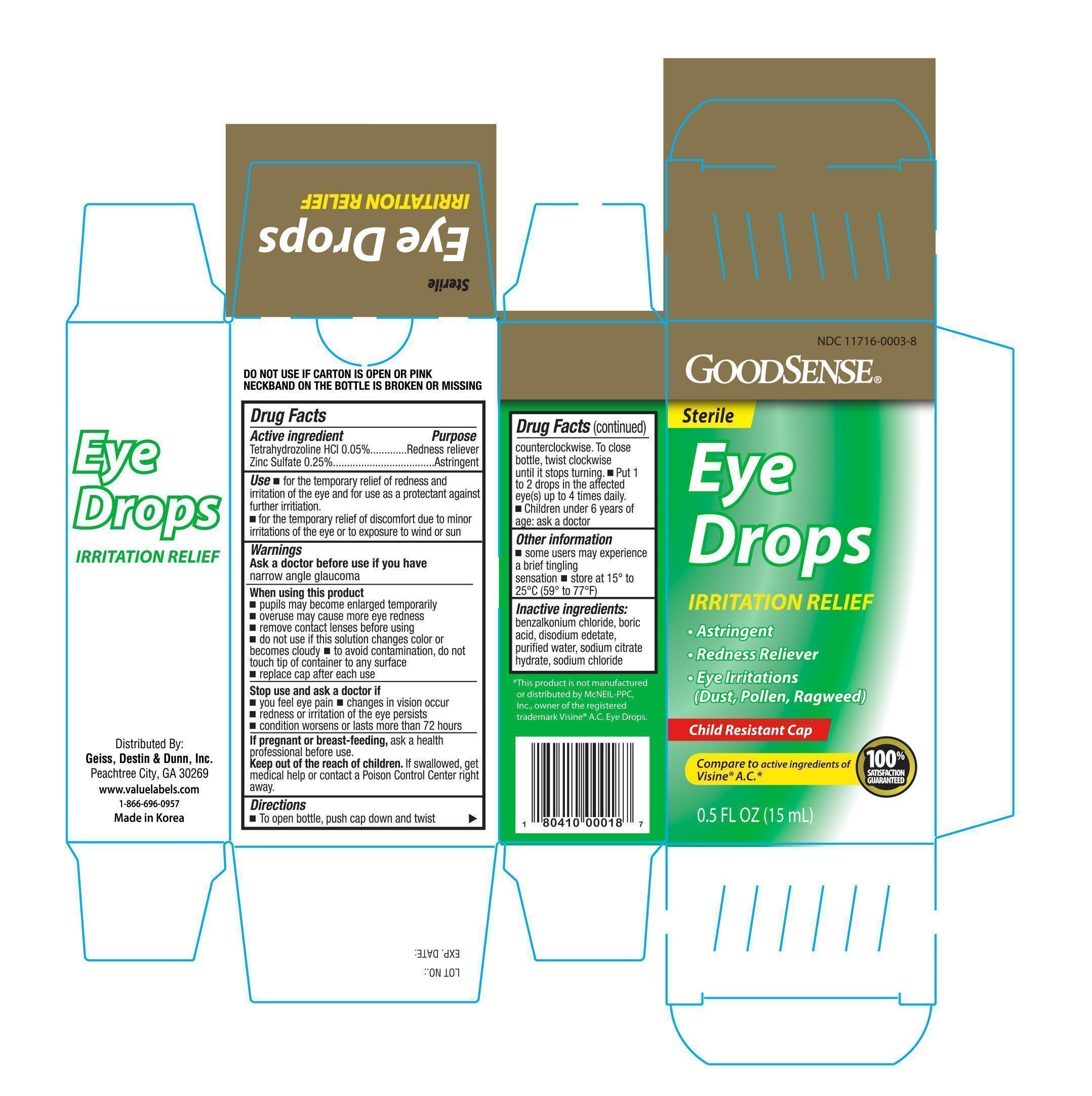 DRUG LABEL: GOODSENSE IRRITATION RELIEF EYE
NDC: 11716-0003 | Form: SOLUTION/ DROPS
Manufacturer: HANLIM PHARM. CO., LTD.
Category: otc | Type: HUMAN OTC DRUG LABEL
Date: 20141218

ACTIVE INGREDIENTS: TETRAHYDROZOLINE HYDROCHLORIDE 0.5 mg/1 mL; ZINC SULFATE 2.5 mg/1 mL
INACTIVE INGREDIENTS: BENZALKONIUM CHLORIDE; BORIC ACID; EDETATE DISODIUM; WATER; SODIUM CHLORIDE; SODIUM CITRATE

Active ingredients Purpose

Tetrahydrozoline HCL 0.05%..................................................... Redness Reliever

Zinc Sulfate............................................................................. Astringent

Uses

- for the temporary relief of redness and irritation of the eye and for use as a protectant against further irritation.
- for the temporary relief of discomfort due to minor irritations of the eye or to exposure to wind or sun.

Warnings

Ask a doctor before use if you have narrow angle glaucoma

When using this product

- pupils may become enlarged temporarily
- overuse may cause more eye redness
- remove contact lenses before using
- do not use if this solution change color or becomes cloudy
- do not touch tip of container to any surface to avoid contamination
- replace cap after each use

Stop use and ask a doctor if

- you feel eye pain
- changes in vision occur
- redness or irritation of the eye persists
- condition worsens or lasts more than 72 hours

PREGNANCY OR BREAST FEEDING

If pregnant or breast-feeding, ask a health professional before use.

Keep out of the reach of children.

If swallowed, get medical help or contact a Poison Control Center right away

Directions

- To open bottle, push cap down and twist counterclockwise. To close bottle, twist clockwise until it stops turning
- Put 1 to 2 drops in the affected eye(s) up to 4 times daily
- Children under 6 years of age: ask a doctor

Other information

- some users may experience a brief tingling
- store at 15° to 25°C (59° to 77°F)

INACTIVE INGREDIENT

Inactive Ingredients: Benzalkonium Chloride, Boric Acid, Edetate Disodium, Purified Water, Sodium Chloride, Sodium Citrate

DOSAGE AND ADMINISTRATION

Distributed By:

Geiss, Destin & Dunn, Inc.

Peachtree City, GA 30269

www.valuelabels.com

1-866-696-0957

Made in Korea